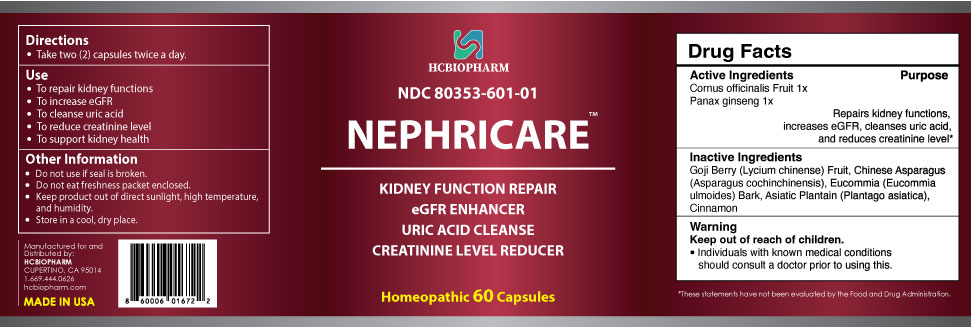 DRUG LABEL: Nephricare
NDC: 80353-601 | Form: CAPSULE
Manufacturer: HCBIOPHARM LLC
Category: homeopathic | Type: HUMAN OTC DRUG LABEL
Date: 20250103

ACTIVE INGREDIENTS: PANAX GINSENG WHOLE 1 [hp_X]/1 1; CORNUS OFFICINALIS FRUIT 1 [hp_X]/1 1
INACTIVE INGREDIENTS: PLANTAGO ASIATICA; CINNAMON; LYCIUM CHINENSE FRUIT; ASPARAGUS COCHINCHINENSIS WHOLE; EUCOMMIA ULMOIDES BARK

Active Ingredients

Cornus officinalis 1X

Panax ginseng 1X

Purpose

Repairs kidney functions, increases eGFR, cleanses uric acid, and reduces creatinine level*

Keep out of Reach of Children

Directions

Take two (2) capsules a day.

Use

- To repair kidney functions
- To increase eGFR
- To cleanse uric acid
- To reduce creatinine level
- To support kidney health

Inactive Ingredients

Japanese Cornelian Cherry (Lycium chinense) Fruit, Chinese Asparagus (Asparagus cochinchinensis),
Eucommia (Eucommia ulmoides) Bark, Asiatic Plantain (Plantago asiatica), Cinnamon

Warning

Individuals with known medical conditions should consult a doctor prior to using this.

Other Information

- Do not use if seal is broken.
- Do not eat freshness packet enclosed.
- Keep product out of direct sunlight, high temperature, and humidity.
- Store in a cool, dry place.

Package Label Display

Nephricare

KIDNEY FUNCTION REPAIR
eGFR ENHANCER
URIC ACID CLEANSE
CREATININE LEVEL REDUCER

Homeopathic 60 Capsules